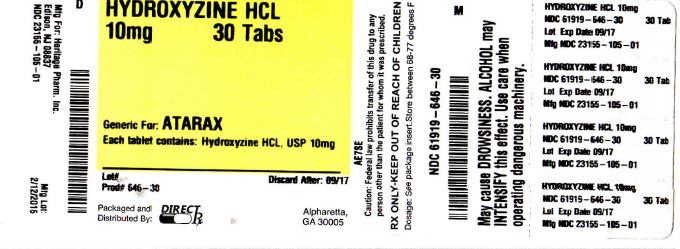 DRUG LABEL: HYDROXYZINE HCL
NDC: 61919-646 | Form: TABLET, FILM COATED
Manufacturer: DIRECT RX
Category: prescription | Type: HUMAN PRESCRIPTION DRUG LABEL
Date: 20200120

ACTIVE INGREDIENTS: HYDROXYZINE HYDROCHLORIDE 10 mg/1 1
INACTIVE INGREDIENTS: LACTOSE MONOHYDRATE; HYPROMELLOSES; SILICON DIOXIDE; MAGNESIUM STEARATE; CELLULOSE, MICROCRYSTALLINE; SODIUM STARCH GLYCOLATE TYPE A POTATO; STEARIC ACID; POLYSORBATE 80; TITANIUM DIOXIDE; POLYETHYLENE GLYCOL, UNSPECIFIED

HYDROXYZINE HCL

DESCRIPTION

HydrOXYzine hydrochloride has the chemical name of 2-[2-[4- (p-Chloro-α-phenylbenzyl)-1-piperazinyl] ethoxy] ethanol dihydrochloride.

[31945055-figure-01]

C21H27CIN202.2HCI

HydrOXYzine hydrochloride occurs as a white, odorless powder which is very soluble in water.

Each tablet for oral administration contains 10 mg, 25 mg or 50 mg hydrOXYzine HCl. Inactive ingredients include: lactose monohydrate, colloidal silicon dioxide, hypromellose, magnesium stearate, microcrystalline cellulose, sodium starch glycolate, stearic acid, polyethylene glycol, polysorbate 80, and titanium dioxide.

CLINICAL PHARMACOLOGY

HydrOXYzine hydrochloride is unrelated chemically to the phenothiazines, reserpine, meprobamate or the benzodiazepines. HydrOXYzine is not a cortical depressant, but its action may be due to a suppression of activity in certain key regions of the subcortical area of the central nervous system.

Primary skeletal muscle relaxation has been demonstrated experimentally. Bronchodilator activity, and antihistaminic and analgesic effects have been demonstrated experimentally and confirmed clinically. An antiemetic effect, both by the apomorphine test and the veriloid test, has been demonstrated.

Pharmacological and clinical studies indicate that hydrOXYzine in therapeutic dosage does not increase gastric secretion or acidity and in most cases has mild antisecretory activity.

HydrOXYzine is rapidly absorbed from the gastrointestinal tract and hydrOXYzine’s clinical effects are usually noted within 15 to 30 minutes after oral administration.

INDICATIONS AND USAGE

For symptomatic relief of anxiety and tension associated with psychoneurosis and as an adjunct in organic disease states in which anxiety is manifested.

Useful in the management of pruritus due to allergic conditions such as chronic urticaria and atopic and contact dermatoses, and in histamine-mediated pruritus.

As a sedative when used as a premedication and following general anesthesia, hydrOXYzine may potentiate meperidine and barbiturates, so their use in pre-anesthetic adjunctive therapy should be modified on an individual basis. Atropine and other belladonna alkaloids are not affected by the drug. HydrOXYzine is not known to interfere with the action of digitalis in any way and it may be used concurrently with this agent.

The effectiveness of hydrOXYzine as an antianxiety agent for long term use, that is more than 4 months, has not been assessed by systematic clinical studies. The physician should reassess periodically the usefulness of the drug for the individual patient.

CONTRAINDICATIONS

Oral hydroxyzine hydrochloride is contraindicated in patients with known hypersensitivity to hydroxyzine hydrochloride products, and in patients with known hypersensitivity to cetirizine hydrochloride or levocetirizine hydrochloride.

HydrOXYzine, when administered to the pregnant mouse, rat, and rabbit induced fetal abnormalities in the rat and mouse at doses substantially above the human therapeutic range. Clinical data in human beings are inadequate to establish safety in early pregnancy. Until such data are available, hydrOXYzine is contraindicated in early pregnancy.

HydrOXYzine is contraindicated for patients who have shown a previous hypersensitivity to it.

WARNINGS: Nursing Mothers: It is not known whether this drug is excreted in human milk. Since many drugs are so excreted, hydrOXYzine should not be given to nursing mothers.

PRECAUTIONS

THE POTENTIATING ACTION OF HYDROXYZINE MUST BE CONSIDERED WHEN THE DRUG IS USED IN CONJUNCTION WITH CENTRAL NERVOUS SYSTEM DEPRESSANTS SUCH AS NARCOTICS, NON-NARCOTIC ANALGESICS AND BARBITURATES. Therefore, when central nervous system depressants are administered concomitantly with hydrOXYzine their dosage should be reduced.

Since drowsiness may occur with use of this drug, patients should be warned of this possibility and cautioned against driving a car or operating dangerous machinery while taking hydrOXYzine. Patients should also be advised against the simultaneous use of other CNS depressant drugs, and cautioned that the effects of alcohol may be increased.

Geriatric Use: A determination has not been made whether controlled clinical studies of hydrOXYzine included sufficient numbers of subjects aged 65 and over to define a difference in response from younger subjects. Other reported clinical experience has not identified differences in responses between the elderly and younger patients. In general, dose selection for an elderly patient should be cautious, usually starting at the low end of the dosing range, reflecting the greater frequency of decreased hepatic, renal or cardiac function, and of concomitant disease or other drug therapy.

The extent of renal excretion of hydrOXYzine has not been determined. Because elderly patients are more likely to have decreased renal function, care should be taken in dose selections.

Sedating drugs may cause confusion and over sedation in the elderly; elderly patients generally should be started on low doses of hydrOXYzine and observed closely.

ADVERSE REACTIONS

Side effects reported with the administration of hydrOXYzine hydrochloride are usually mild and transitory in nature.

Anticholinergic: Dry mouth.

Central Nervous System: Drowsiness is usually transitory and may disappear in a few days of continued therapy or upon reduction of dose. Involuntary motor activity including rare instances of tremor and convulsions have been reported, usually with doses considerably higher than those recommended. Clinically significant respiratory depression has not been reported at recommended doses.

In post-marketing experience, the following additional undesirable effects have

been reported:

Body as a Whole: Allergic reaction.

Nervous System: Headache.

Psychiatric: Hallucination.

Skin and Appendages: Oral hydroxyzine hydrochloride is associated with fixed drug eruptions in postmarketing reports.

OVERDOSAGE

The most common manifestation of hydrOXYzine overdosage is hypersedation. As in the management of overdosage with any drug, it should be borne in mind that multiple agents may have been taken.

If vomiting has not occurred spontaneously, it should be induced. Immediate gastric lavage is also recommended. General supportive care, including frequent monitoring of the vital signs and close observation of the patient, is indicated. Hypotension, though unlikely, may be controlled with intravenous fluids and levarterenol or metaraminol. Do not use epinephrine as hydrOXYzine counteracts its pressor action.

There is no specific antidote. It is doubtful that hemodialysis would be of any value in the treatment of overdosage with hydrOXYzine. However, if other agents such as barbiturates have been ingested concomitantly, hemodialysis may be indicated. There is no practical method to quantitate hydrOXYzine in body fluids or tissue after its ingestion or administration.

DOSAGE AND ADMINISTRATION

For symptomatic relief of anxiety and tension associated with psychoneurosis and as an adjunct in organic disease states in which anxiety is manifested: Adults, 50-100 mg q.i.d.; children under 6 years, 50 mg daily in divided doses; children over 6 years, 50-100 mg daily in divided doses.

For use in the management of pruritus due to allergic conditions such as chronic urticaria and atopic and contact dermatoses and in histamine-mediated pruritus: adults, 25 mg t.i.d. or q.i.d.; children under 6 years, 50 mg daily in divided doses; children over 6 years, 50-100 mg daily in divided doses.

As a sedative when used as a premedication and following general anesthesia: 50-100 mg for adults and 0.6 mg/kg of body weight in children.

When treatment is initiated by the intramuscular route of administration, subsequent doses may be administered orally.

As with all potent medication, the dosage should be adjusted according to the patient’s response to therapy.

HOW SUPPLIED

HydrOXYzine Hydrochloride Tablets, USP,

10 mg - Round, white, film-coated tablet, debossed “H/105”, supplied in bottles of 100, 500, and 1000.

Bottles of 100 NDC 23155-105-01

Bottles of 500 NDC 23155-105-05

Bottles of 1000 NDC 23155-105-10

25 mg - Round, white, film-coated tablet, debossed “H/106”, supplied in bottles of 100, 500, and 1000.

Bottles of 100 NDC 23155-106-01

Bottles of 500 NDC 23155-106-05

Bottles of 1000 NDC 23155-106-10

50 mg- Round, white, film-coated tablet, debossed “H/107”, supplied in bottles of 100, 500, and 1000.

Bottles of 100 NDC 23155-107-01

Bottles of 500 NDC 23155-107-05

Bottles of 1000 NDC 23155-107-10

Dispense in a tight container as defined in the USP.

Store at controlled room temperature 20°-25°C (68°-77°F); [see USP Controlled Room Temperature].

Call your doctor for medical advice about side effects. You may report side effects to FDA at 1-800-FDA-1088.